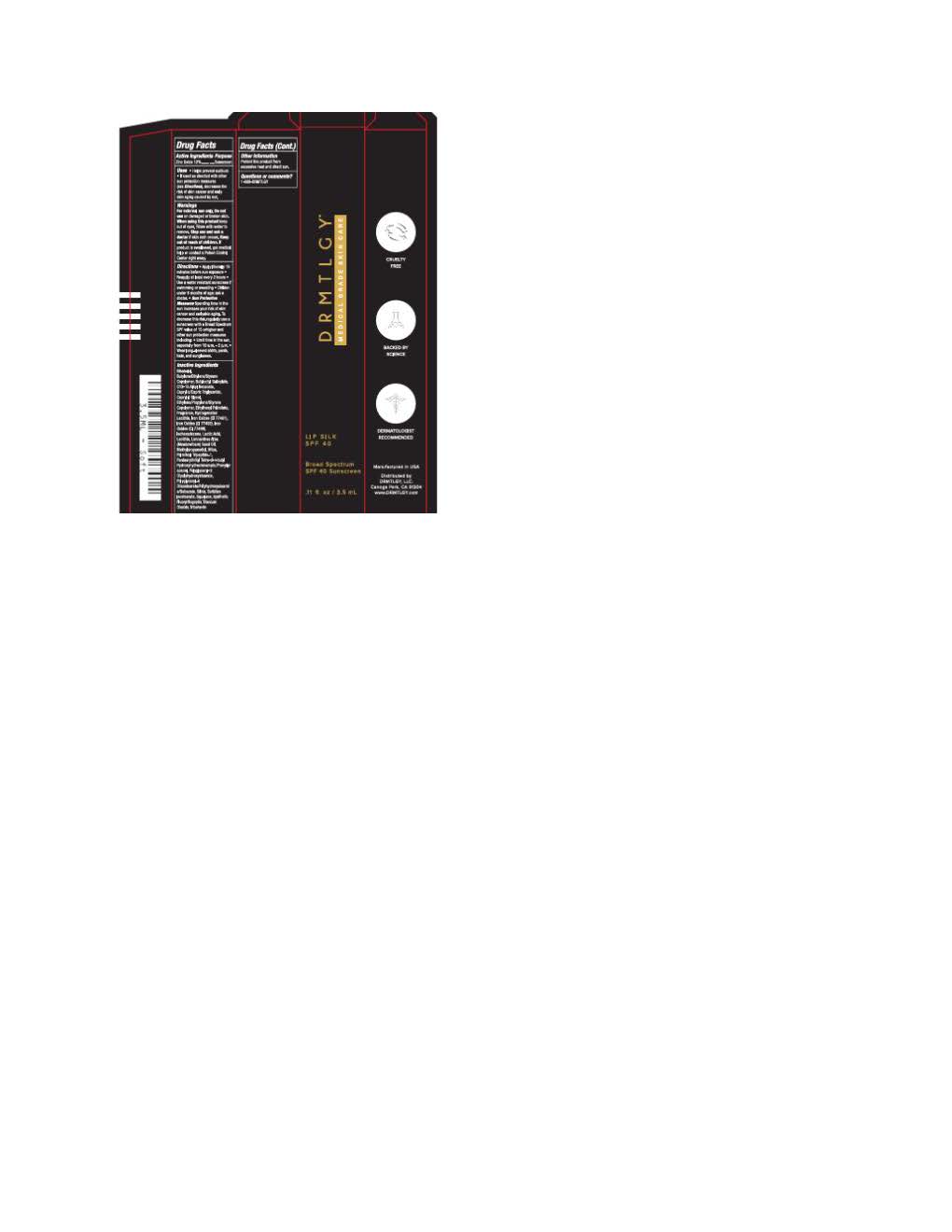 DRUG LABEL: DRMTLGY Lip Silk
NDC: 83286-213 | Form: LOTION
Manufacturer: DRMTLGY
Category: otc | Type: HUMAN OTC DRUG LABEL
Date: 20250924

ACTIVE INGREDIENTS: ZINC OXIDE 132 mg/1 mL
INACTIVE INGREDIENTS: SILICON DIOXIDE; ISOHEXADECANE; TITANIUM DIOXIDE; LECITHIN, SOYBEAN; FERRIC OXIDE YELLOW; FERROSOFERRIC OXIDE; PHENYLPROPANOL; FERRIC OXIDE RED; ALKYL (C12-15) BENZOATE; CAPRYLIC/CAPRIC TRIGLYCERIDE; CAPRYLYL GLYCOL; POLYGLYCERYL-4 DIISOSTEARATE/POLYHYDROXYSTEARATE/SEBACATE; SQUALANE; METHYLPROPANEDIOL; PENTAERYTHRITYL TETRA-DI-T-BUTYL HYDROXYHYDROCINNAMATE; LACTIC ACID; SORBITAN ISOSTEARATE; ETHYLHEXYL PALMITATE; LIMNANTHES ALBA (MEADOWFOAM) SEED OIL; BUTYLOCTYL SALICYLATE; TRIBEHENIN; PALMITOYL TRIPEPTIDE-1; MICA; .ALPHA.-BISABOLOL, (+)-

DRMTLGY Lip Silk